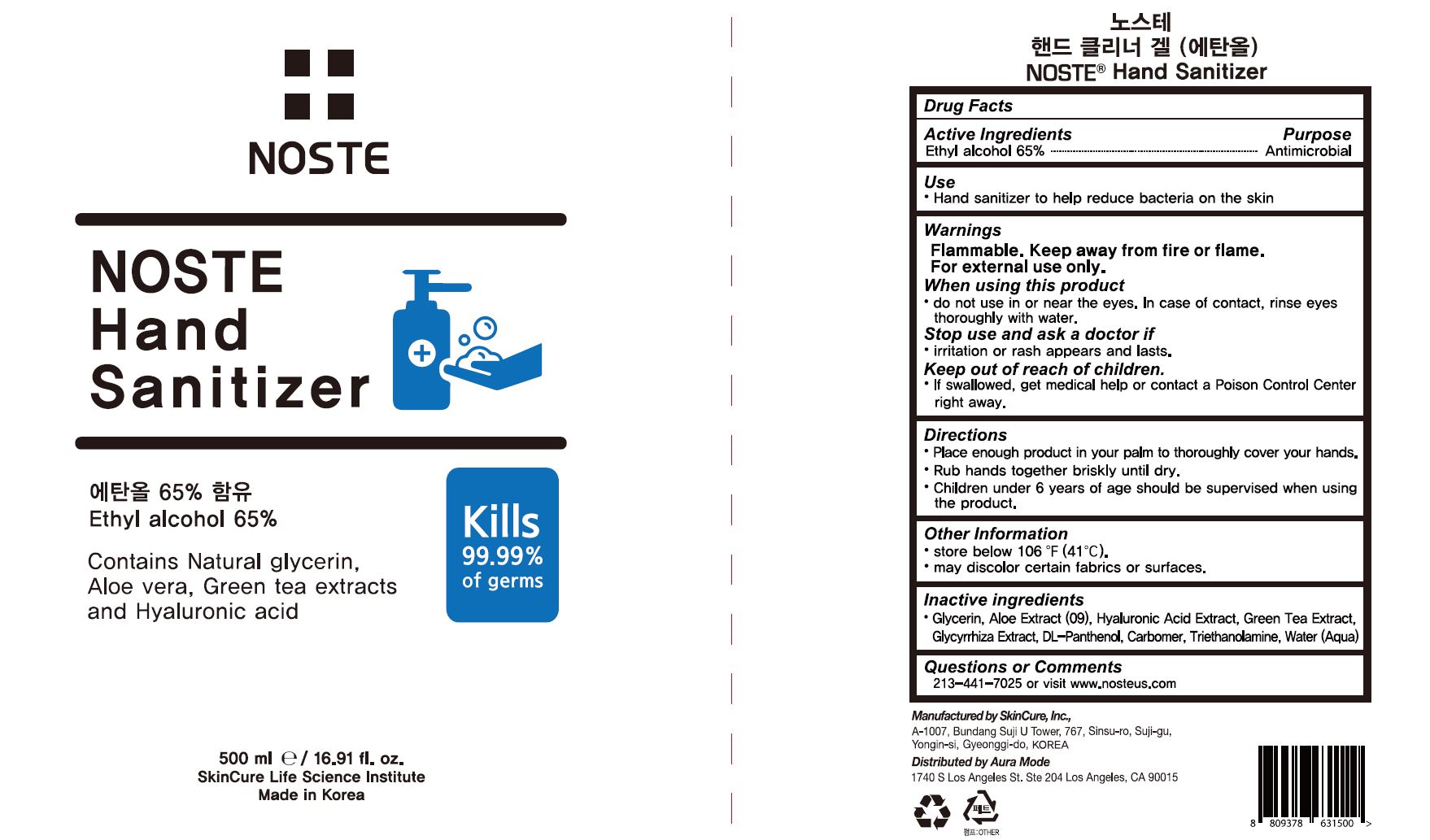 DRUG LABEL: NOSTE Hand Sanitizer
NDC: 72289-0010 | Form: GEL
Manufacturer: SKINCURE INC
Category: otc | Type: HUMAN OTC DRUG LABEL
Date: 20200517

ACTIVE INGREDIENTS: ALCOHOL 65 mL/100 mL
INACTIVE INGREDIENTS: 1,2-HEXANEDIOL; PHENOXYETHANOL; GREEN TEA LEAF; PANTHENOL; GLYCERIN; HYALURONIC ACID (NON-ANIMAL STABILIZED); CAPRYLYL GLYCOL; BUTYLENE GLYCOL; ALOE VERA LEAF; CARBOMER 940; TROLAMINE; WATER; LICORICE

Drug Facts

ACTIVE INGREDIENT

alcohol

INACTIVE INGREDIENT

Water
Glycerin
Hyaluronic Acid Extract
1,2-Hexanediol
Carbomer
Triethanolamine
Aloe Extract(09)
Butylene Glycol
Phenoxyethanol
Green Tea Extract
Glycyrrhiza Extract
DL-Panthenol

PURPOSE

hand sanitizer to help reduce bacteria on the skin

KEEP OUT OF REACH OF THE CHILDREN

INDICATIONS AND USAGE

Apply to clean, dry hands. Apply sufficient amount to thoroughly wet all surfaces of hands and fingers. Rub onto hands until dry.

Supervise children in the use of this product.

WARNINGS

■ Flammable. Keep away from fire or flame.

■ For external use only.

■ Do not use in eyes.

■ lf swallowed, get medical help promptly.

■ Stop use, ask doctor lf irritation occurs.

■ Keep out of reach of children.

DOSAGE AND ADMINISTRATION

for external use only